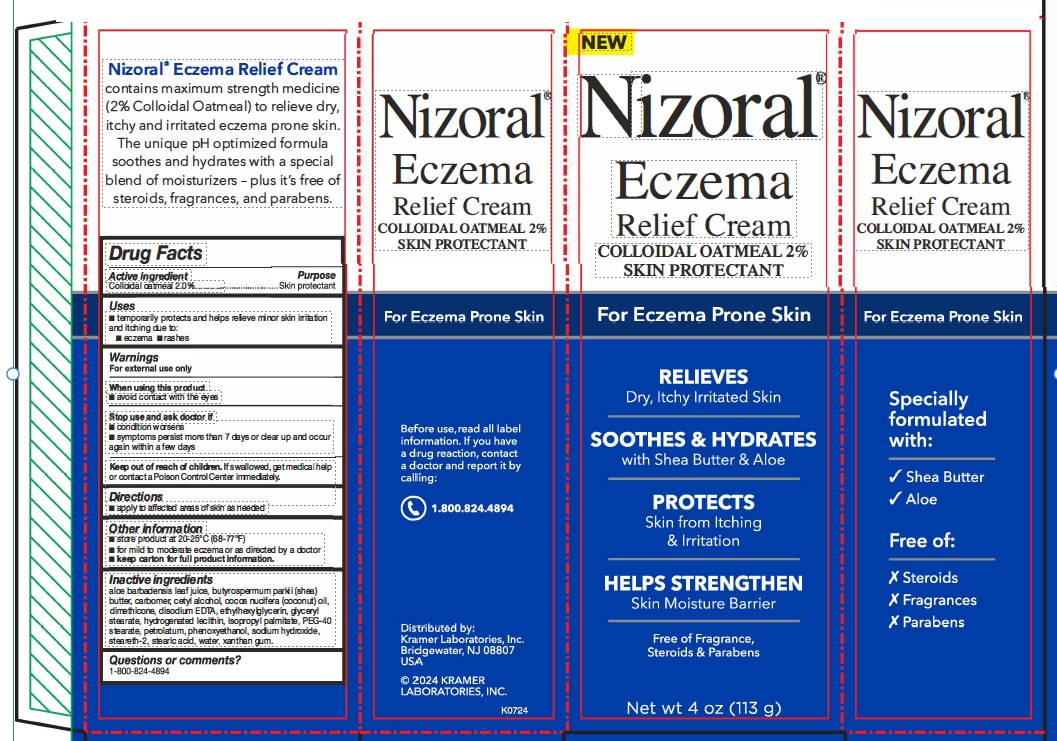 DRUG LABEL: Nizoral Eczema Relief Cream
NDC: 55505-223 | Form: CREAM
Manufacturer: Kramer Laboratories
Category: otc | Type: HUMAN OTC DRUG LABEL
Date: 20251223

ACTIVE INGREDIENTS: Oatmeal 2 g/100 g
INACTIVE INGREDIENTS: Aloe Vera Leaf; Shea Butter; Carbomer Homopolymer, Unspecified Type; Cetyl Alcohol; Coconut Oil; Dimethicone; Edetate Disodium; Ethylhexylglycerin; Glyceryl Monostearate; Hydrogenated Soybean Lecithin; Isopropyl Palmitate; Peg-40 Monostearate; Petrolatum; Phenoxyethanol; Sodium Hydroxide; Steareth-2; Stearic Acid; Water; Xanthan Gum

Drug Facts

ACTIVE INGREDIENT

Active ingredient | Purpose
Colloidal oatmeal 2.0% | Skin protectant

Uses

- temporarily protects and helps relieve minor skin irritation and itching due to:
  - eczema
  - rashes

Warnings
For external use only

When using this product

- avoid contact with the eyes

Stop use and ask a doctor if

- condition worsens
- symptoms persist for more than 7 days or clear up and occur again within a few days

KEEP OUT OF REACH OF CHILDREN

Keep out of the reach of children. If swallowed, get medical help or contact a Poison Control Center immediately.

Directions

- apply to affected areas of skin as needed

Other information

- store product at 20-25°C (68-77°F)
- for mild to moderate eczema or as directed by a doctor
- keep carton for full product information.

Inactive ingredients

aloe barbadensis leaf juice, butyrospermum parksii (shea)
butter, carbomer, cetyl alcohol, cocos nucifera (coconut) oil,
dimethicone, disodium EDTA, ethylhexylglycerin, glyceryl
stearate, hydrogenated lecithin, isopropyl palmitate, PEG-40
stearate, petrolatum, phenoxyethanol, sodium hydroxide,
steareth-2, stearic acid, water, xanthan gum.

Questions or comments?
1-800-824-4894

PRINCIPAL DISPLAY PANEL

New
Nizoral®
Eczema
Relief Cream
COLLOIDAL OATMEAL 2%
SKIN PROTECTANT
For Eczema Prone Skin
RELIEVES
Dry, Itchy Irritated Skin
SOOTHES & HYDRATES
with Shea Butter & Aloe
PROECTS
Skin from Itching
& Irritation
HELPS STRENGTHEN
Skin Moisture Barrier
Free of Fragrance,
Steroids & Parabens
Net wt 4 oz (113 g)
Specially
formulated with:
√ Shea Butter
√ Aloe
Free of:
Ⅹ Steroids
Ⅹ Fragrances
Ⅹ Parabens
Before use, read all label
information. If you have
a drug reaction, contact
a doctor and report it by
calling:
1.800.824.4894
Distributed by:
Kramer Laboratories, Inc.
Bridgewater, NJ 08807
USA
© 2024 KRAMER
LABORATORIES, INC.
K0724